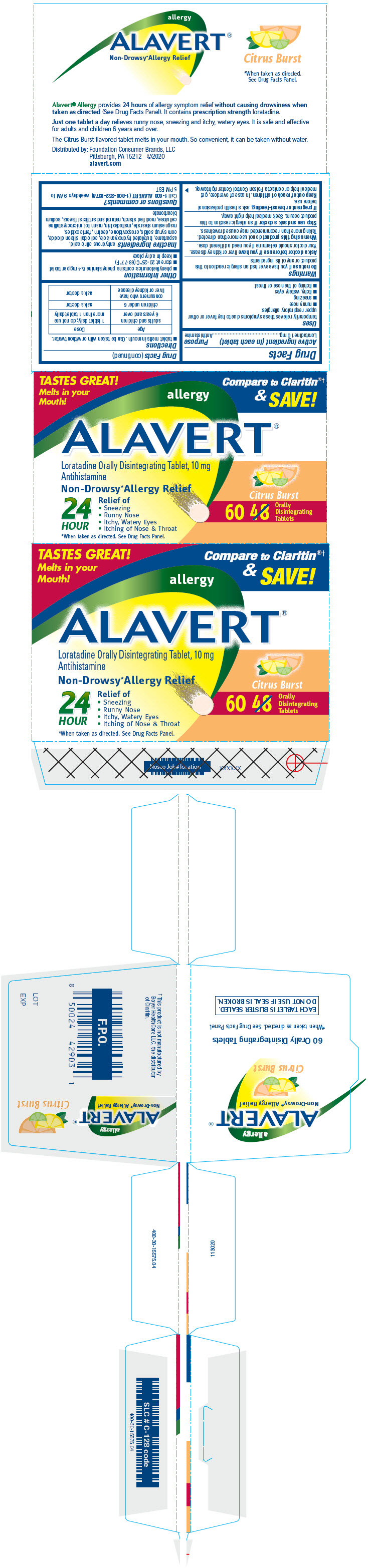 DRUG LABEL: Alavert
NDC: 80070-110 | Form: TABLET, ORALLY DISINTEGRATING
Manufacturer: Foundation Consumer Brands
Category: otc | Type: HUMAN OTC DRUG LABEL
Date: 20260223

ACTIVE INGREDIENTS: LORATADINE 10 mg/1 1
INACTIVE INGREDIENTS: ASPARTAME; BUTYLATED HYDROXYANISOLE; MICROCRYSTALLINE CELLULOSE; CORN SYRUP; CROSPOVIDONE (120 .MU.M); ICODEXTRIN; FERRIC OXIDE RED; ANHYDROUS CITRIC ACID; FERRIC OXIDE YELLOW; MAGNESIUM STEARATE; MALTODEXTRIN; MANNITOL; SILICON DIOXIDE; SODIUM BICARBONATE

Alavert®
Allergy

Drug Facts

Active ingredient (in each tablet)

Loratadine 10 mg

Purpose

Antihistamine

Uses

temporarily relieves these symptoms due to hay fever or other upper respiratory allergies:

- runny nose
- sneezing
- itchy, watery eyes
- itching of the nose or throat

Warnings

DO NOT USE

Do not useif you have ever had an allergic reaction to this product or any of its ingredients

Ask a doctor before use if you haveliver or kidney disease. Your doctor should determine if you need a different dose.

WHEN USING

When using this productdo not use more than directed. Taking more than recommended may cause drowsiness.

Stop use and ask a doctor ifan allergic reaction to this product occurs. Seek medical help right away.

PREGNANCY OR BREAST FEEDING

If pregnant or breast-feeding,ask a health professional before use.

Keep out of reach of children.In case of overdose, get medical help or contact a Poison Control Center right away.

Directions

- tablet melts in mouth. Can be taken with or without water.
  Age | Dose
  adults and children 6 years and over | 1 tablet daily; do not use more than 1 tablet daily
  children under 6 | ask a doctor
  consumers who have liver or kidney disease | ask a doctor

Other information

- phenylketonurics: contains phenylalanine 8.4 mg per tablet
- store at 20-25°C (68-77°F)
- keep in a dry place

Inactive ingredients

anhydrous citric acid, aspartame, butylated hydroxyanisole, colloidal silicon dioxide, corn syrup solids, crospovidone, dextrin, ferric oxides, magnesium stearate, maltodextrin, mannitol, microcrystalline cellulose, modified starch, natural and artificial flavors, sodium bicarbonate

Questions or comments?

Call 1-800 ALAVERT (1-800-252-8378)weekdays 9 AM to 5 PM EST

Distributed by: Foundation Consumer Brands, LLC
Pittsburgh, PA 15212

PRINCIPAL DISPLAY PANEL - 60 Tablet Blister Pack Carton

TASTES GREAT!
Melts in your
Mouth!

Compare to Claritin®†
&
SAVE!

allergy

ALAVERT®

Loratadine Orally Disintegrating Tablet, 10 mg
Antihistamine

Non-Drowsy* Allergy Relief

24
HOUR

Relief of

- Sneezing
- Runny Nose
- Itchy, Watery Eyes
- Itching of Nose & Throat

*When taken as directed. See Drug Facts Panel.

Citrus Burst

60
Orally
Disintegrating
Tablets